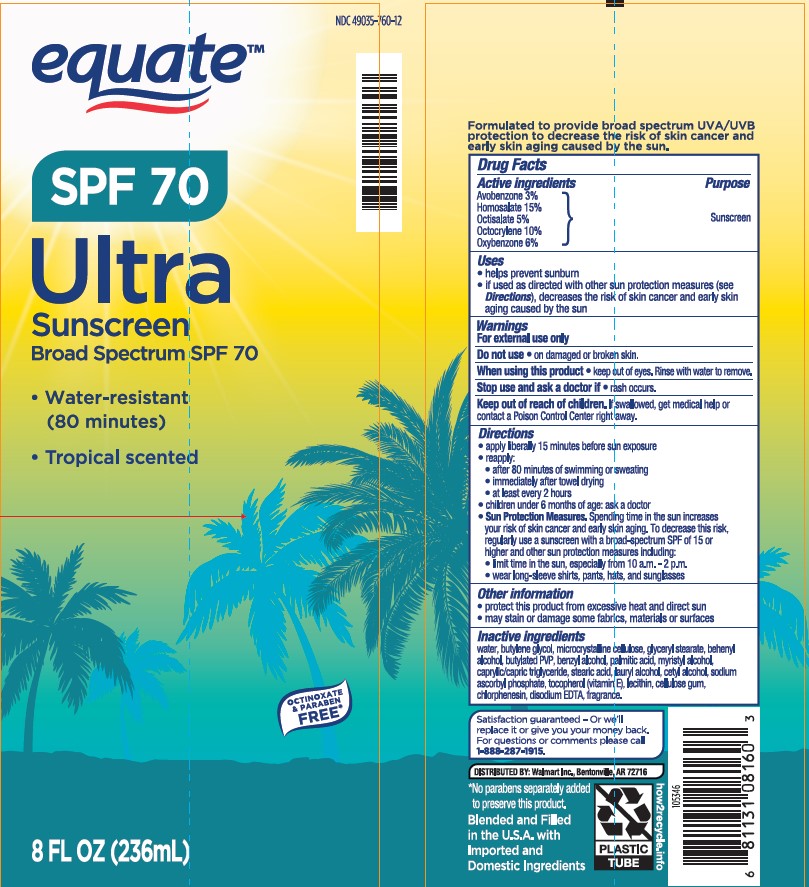 DRUG LABEL: Equate
NDC: 49035-760 | Form: LOTION
Manufacturer: Wal-Mart Stores Inc
Category: otc | Type: HUMAN OTC DRUG LABEL
Date: 20241016

ACTIVE INGREDIENTS: OXYBENZONE 60 mg/1 mL; HOMOSALATE 150 mg/1 mL; OCTISALATE 50 mg/1 mL; OCTOCRYLENE 100 mg/1 mL; AVOBENZONE 30 mg/1 mL
INACTIVE INGREDIENTS: WATER; GLYCERYL MONOSTEARATE; MICROCRYSTALLINE CELLULOSE; MEDIUM-CHAIN TRIGLYCERIDES; PALMITIC ACID; CETYL ALCOHOL; CHLORPHENESIN; N-VINYLPYRROLIDINONE; BUTYLENE GLYCOL; DOCOSANOL; STEARIC ACID; LAURYL ALCOHOL; MYRISTYL ALCOHOL; CARBOXYMETHYLCELLULOSE SODIUM, UNSPECIFIED FORM; LECITHIN, SOYBEAN; TOCOPHEROL; BENZYL ALCOHOL; EDETATE DISODIUM ANHYDROUS; SODIUM ASCORBYL PHOSPHATE

Walmart Equate SPF 70 Ultra Sunscreen Lotion

Active ingredients

Avobenzone 3.0%, Homosalate 15.0%, Octisalate 5.0%, Octocrylene 10.0%, Oxybenzone 6.0%

Purpose

Sunscreen

Uses

- helps prevent sunburn
- if used as directed with other sun protection measures (see Directions), decreases the risk of skin cancer and early aging caused by the sun

Warnings

For external use only

Do not use

• on damaged or broken skin.

When using this product

• keep out of eyes. Rinse with water to remove.

Stop use and ask a doctor if

• rash occurs.

Keep out of reach of children.

If swallowed, get medical help or contact a Poison Control Center right away.

Directions

- apply liberally 15 minutes before sun exposure.
- reapply:
- after 80 minutes of swimming or sweating
- immediately after towel drying
- at least every 2 hours
- children under 6 months of age: Ask a doctor
- Sun Protection Measures. Spending time in the sun increases your risk of skin cancer and early skin aging. To decrease this risk, regularly use a sunscreen with a Broad Spectrum SPF value of 15 or higher and other sun protection measures including:
- limit time in the sun, especially from 10 a.m. – 2 p.m.
- wear long-sleeved shirts, pants, hats, and sunglasses

Other information

- protect the product in this container from excessive heat and direct sun
- may stain or damage some fabrics, materials or surfaces

Inactive ingredients

water, butylene glycol, microcrystalline cellulose, glyceryl stearate, behenyl alcohol, butylated PVP, benzyl alcohol, palmitic acid, myristyl alcohol, caprylic/capric triglyceride, stearic acid, lauryl alcohol, cetyl alcohol, sodium ascorbyl phosphate, tocopherol (vitamin E), lecithin, cellulose gum, chlorphenesin, disodium EDTA, fragrance.